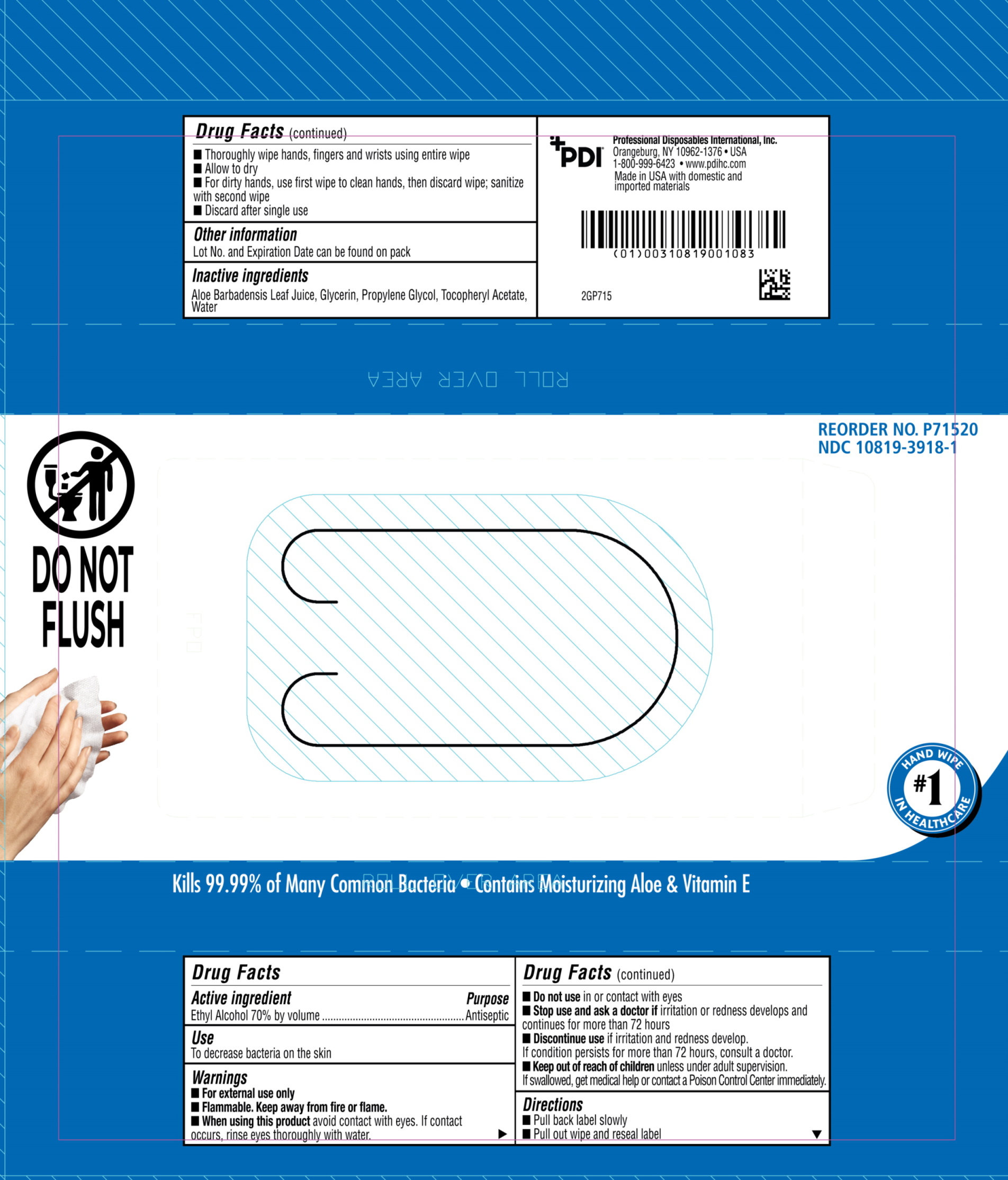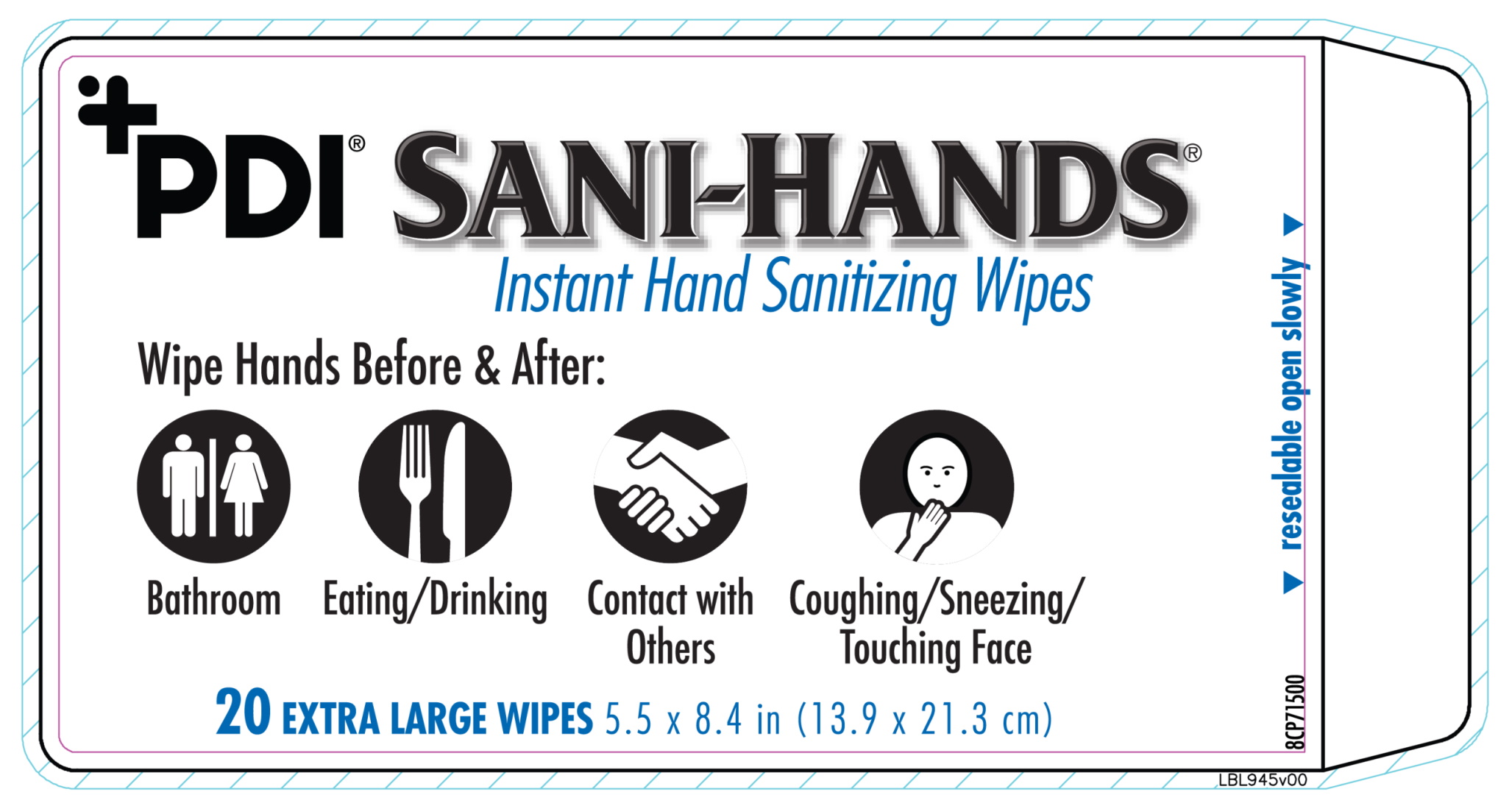 DRUG LABEL: PDI Sani Hands
NDC: 10819-3918 | Form: CLOTH
Manufacturer: Professional Disposables International Inc
Category: otc | Type: HUMAN OTC DRUG LABEL
Date: 20250701

ACTIVE INGREDIENTS: ALCOHOL 0.7 mL/1 mL
INACTIVE INGREDIENTS: WATER; PROPYLENE GLYCOL; ALOE VERA LEAF; ALPHA-TOCOPHEROL ACETATE; GLYCERIN

Sani-Hands Bedside Pack NDC 10819-3918-1

Active ingredient

Alcohol 70% by volume

Purpose

Antiseptic

Uses

- Antiseptic.
- For handwashing to decrease bacteria on the skin.
- Recommended for repeated use.
- Dries in seconds.

Warnings

- Flammable, keep away from fire or flame.
- For external use only.
- Do not use in or contact the eyes.
- Discontinue use if irritation and redness develop. If conditions persist for more than 72 hours, consult a physician.

Keep this out of reach of children

unless under adult supervision.

if swallowed, get medical help or contact a Poison Control Center immediately

Directions

- Peel back label slowly.
- Pull out wipe and reseal label.
- Unfold and use.
- Wipe hands, fingers, interdigital areas and wrists thoroughly with towelette. Be sure to utilize the entire wipe surface. Allow to dry.
- If hands are visibly soiled or contaminated, use first wipe to clean hands, then discard wipe. Sanitize with a second wipe.
- Discard after single use.

inactive ingredients

Water, Propylene Glycol, Glycerin, Aloe Barbadensis Leaf juice, Tocopheryl Acetate

Principal Display panel

Web:

Reseal: